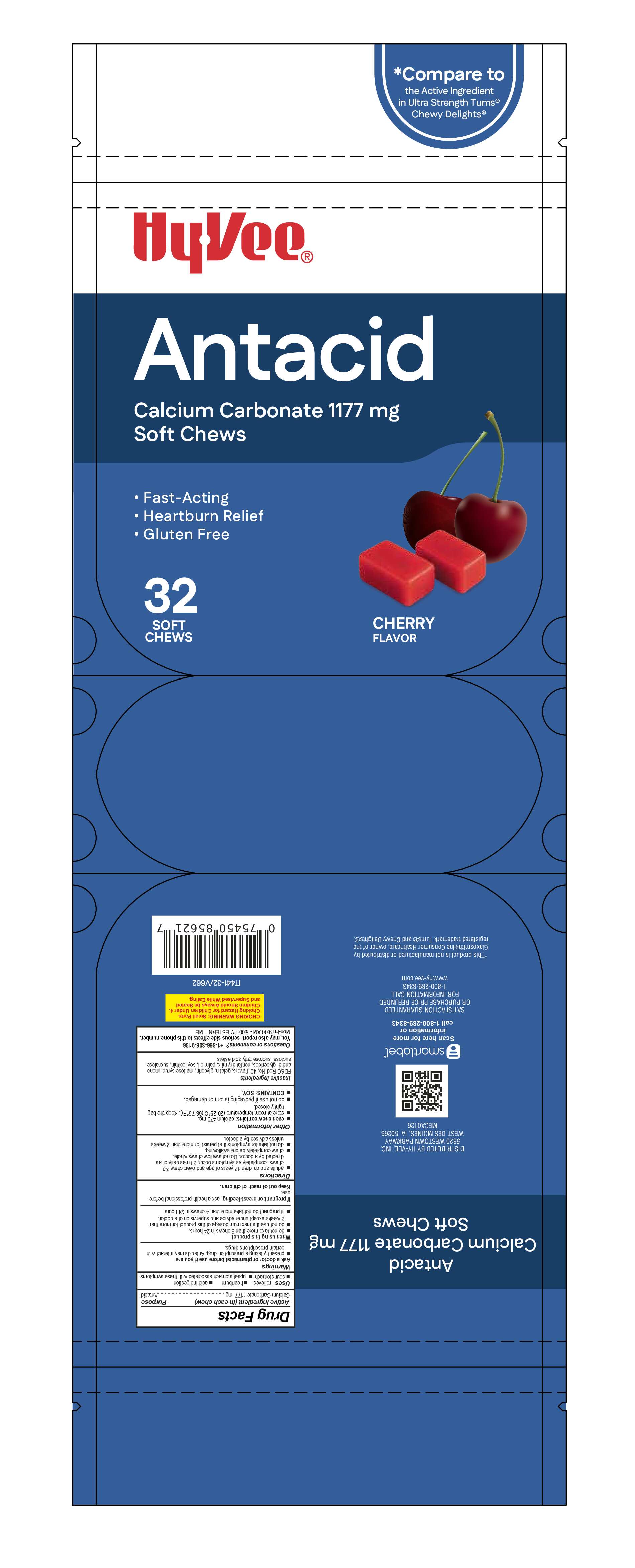 DRUG LABEL: HyVee Ultra Strength Antacid
NDC: 83698-921 | Form: TABLET, CHEWABLE
Manufacturer: Xiamen Kang Zhongyuan Biotechnology Co., Ltd.
Category: otc | Type: HUMAN OTC DRUG LABEL
Date: 20260225

ACTIVE INGREDIENTS: CALCIUM CARBONATE 1177 mg/1 1
INACTIVE INGREDIENTS: GLYCERIN; SUCRALOSE; GELATIN; SUCROSE; LECITHIN, SOYBEAN; SKIM MILK; FD&C RED NO. 40; MALTOSE SYRUP; PALM OIL; C14-18 MONO-AND DI-GLYCERIDES

Xiamen-HyVee Soft Chews

Active ingredient (in each chew)

Calcium carbonate 1,177 mg

Purpose

Antacid

Uses

Relieves

- heartburn
- acid indigestion
- sour stomach
- upset stomach associated with these symptoms

Warnings

Ask a doctor or pharmacist before use if you are

- presently taking a prescription drug. Antacids may interact with certain perscription drugs.

When using this product

- do not take more than 6 chews in 24 hours
- do not use the maximum dosage of this product for more than 2 weeks except under the advice and supervision of a doctor
- if pregnant do not take more than 4 chews in 24 hours

PREGNANCY OR BREAST FEEDING

If pregnant or breast-feeding, ask a health professional before use

Keep out of reach of children.

Directions

- Adults and children 12 years of age and over: chew 2-3 chews, completely as symptoms occur, 2 times daily or as directed by a doctor. Do not swallow chews whole.
- Do not take for symptoms that persist for mare than 2 weeks unless advised by a doctor

Other information

- Each chew contains:calcium 470 mg
- Store at room temperatrue 20-25ºC (68-77ºF). Keep bag tightly closed.
- Do not use if packaging is torn or damaged.
- Contains: soy

Inactive ingredients:

FD&C Red No. 40, Flaors, Gelatin, Glycerin, Soy Lecithin, Maltose Syrup, Mono and Di-glycerides of Fatty Acids, Nonfat dry milk, Palm Oil, Sucralose, Sucrose Fatty Acid Esters.

Questions or comments? +1-866-306-9136
You may also report serious side effects to this phone number.
Mon-Fri 9:00 AM - 5:00 PM ESTERN TIME